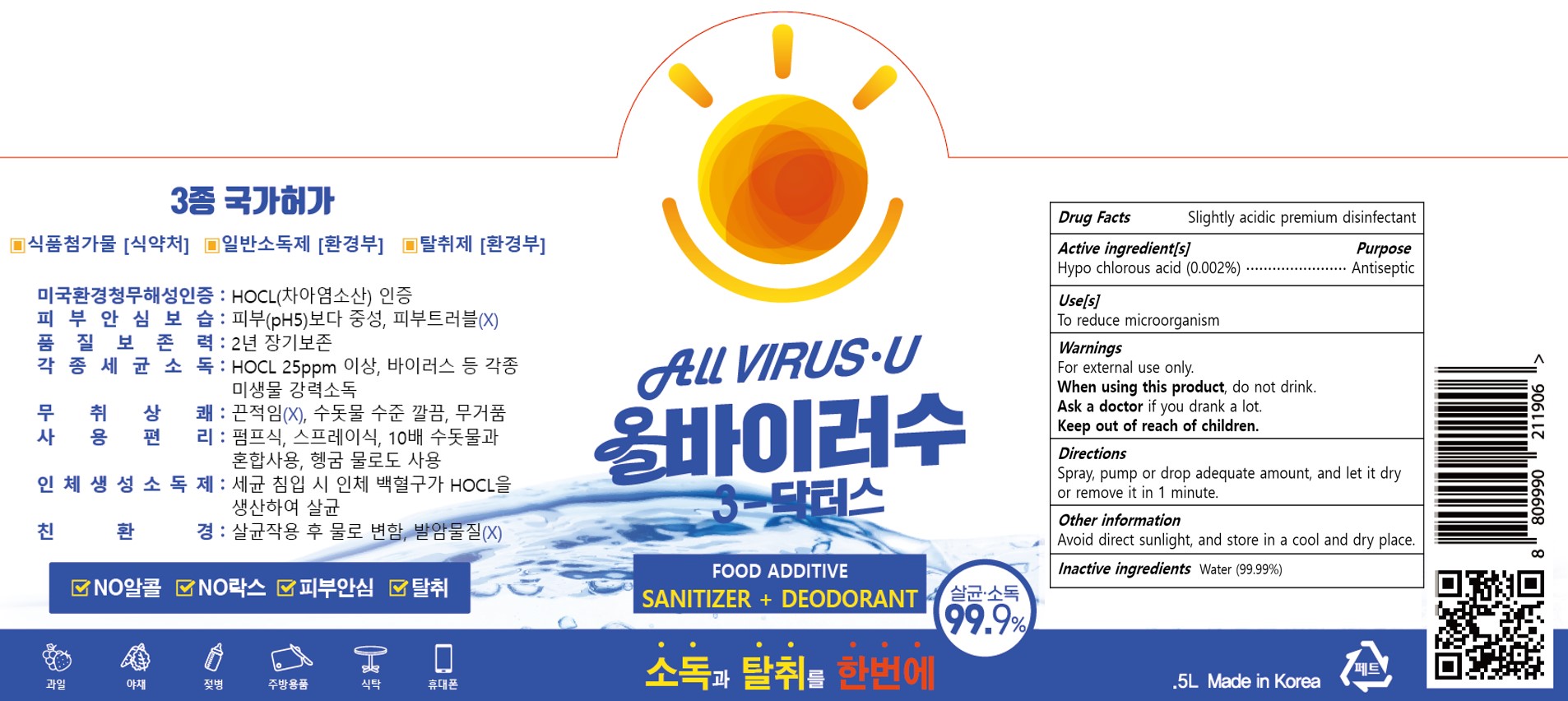 DRUG LABEL: ALLVIRUSU
NDC: 80767-201 | Form: LIQUID
Manufacturer: StarParks
Category: otc | Type: HUMAN OTC DRUG LABEL
Date: 20221227

ACTIVE INGREDIENTS: HYPOCHLOROUS ACID 0.002 g/100 mL
INACTIVE INGREDIENTS: WATER

80767-201

Active ingredient[s]

Hypochlorous acid (0.002%)

Purpose

Antiseptic

Use[s]

To reduce microorganism

Warnings

For external use only.

When using this product

do not drink.

Ask a doctor

if you drank a lot.

Directions

Spray, pump or drop adequate amount, and let it dry or remove it in 1 minute.

Other information

Avoid direct sunlight, and store in a cool and dry place.

Inactive ingredients

Water (99.99%)